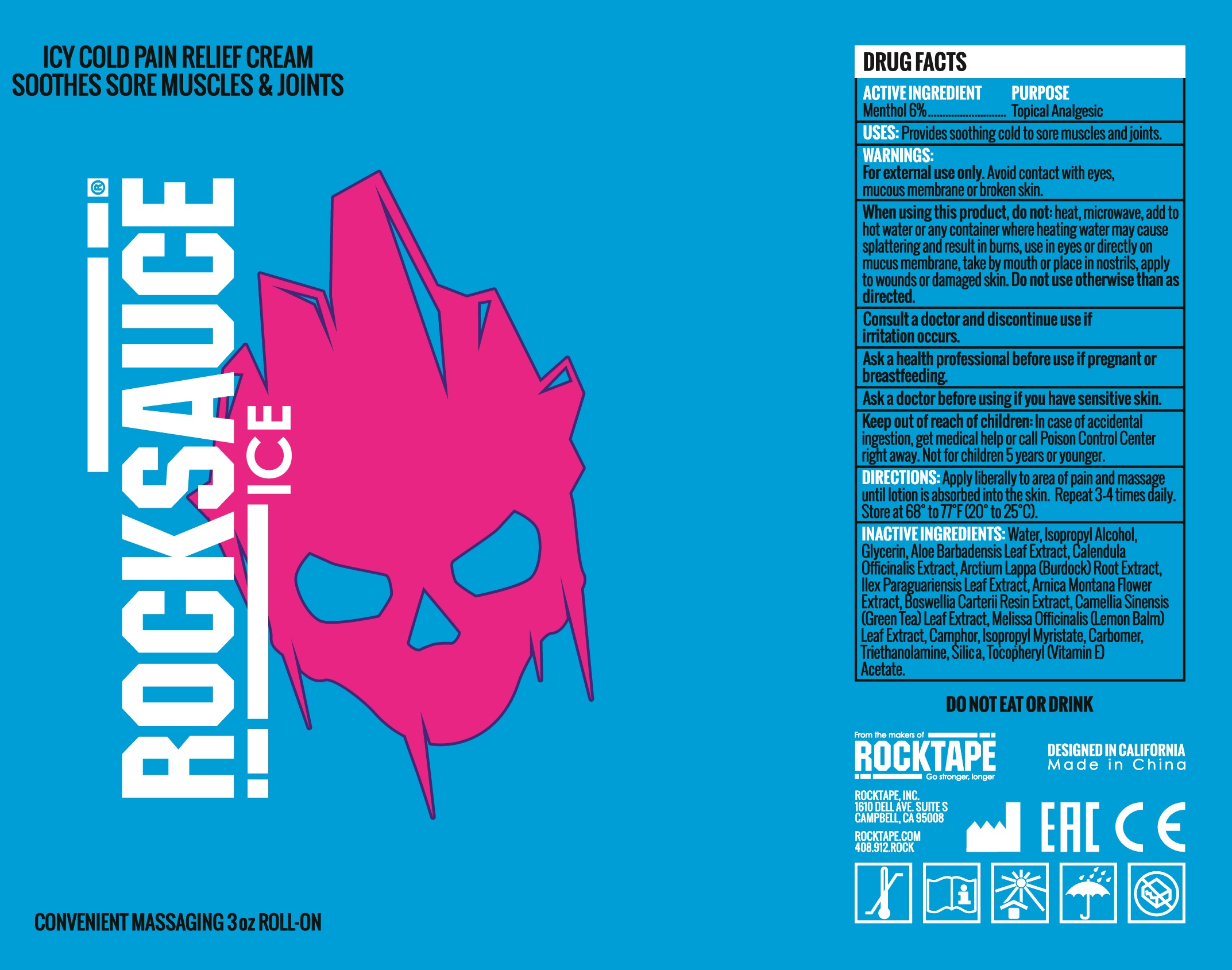 DRUG LABEL: RockSauce ICE
NDC: 73344-102 | Form: GEL
Manufacturer: NINGBO SANTE YING MEDICALAND HEALTHDEVELOPMENT CO.,LTD
Category: otc | Type: HUMAN OTC DRUG LABEL
Date: 20190929

ACTIVE INGREDIENTS: MENTHOL 6.0 g/100 g
INACTIVE INGREDIENTS: ISOPROPYL ALCOHOL; GLYCERIN; ARCTIUM LAPPA ROOT OIL; ARNICA MONTANA FLOWER; MELISSA OFFICINALIS LEAF OIL; ISOPROPYL MYRISTATE

rocksauce ICE

Active Ingredient

Menthol 6.0%

Purpose

Topical Analgesic

Uses

Provides soothing Cold to sore muscles and joints

Warnings

For external use only.

Avoid contac with eyes, Mucous membrance or broken skin.

Consult a doctor and discontinue use

if irritation occurs, ask a health professional before use if pregnant or brastfeeding. before using if you have sensitive skin.

Keep out of reach of children.

if accidental ingestion, get medical help or call a Poison Control Center right away.

Directions

Apply liberally to area of pain and massage unti lotion is absorbed into the skin. Repeat 3-4 times daily. Store at 68° to 77°F (20°to 25°C).

Inactive Ingredients

Water, Isopropyl Alcohol, Glycerin, Aloe Barbadensis Leaf Extract, Calendula Officinalis Extract, Arctium Lappa (Burdock) Root Extract, Illex Paraguariensis Leaf Extract, Arnica Montana Flower Extract, Boswellia Carterii Resin Extract, Camellia Sinensis (Green Tea) Leaf Extract, Melissa Officinalis (Lemon Balm) Leaf Extract, Camphor, Isopropyl Myristate, Carbomer, Triethanolamine, Silica, Tocopheryl (Vitamin E) Acetate

PACKAGE LABEL

RockSauce ICE

Net wt 3 oz

DISTRIBUTED BY:

Rocktape, Inc

questions: please contact 408-912-7625

made in china